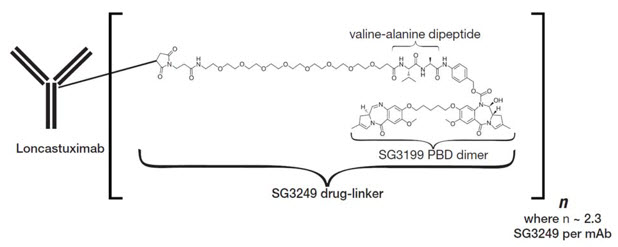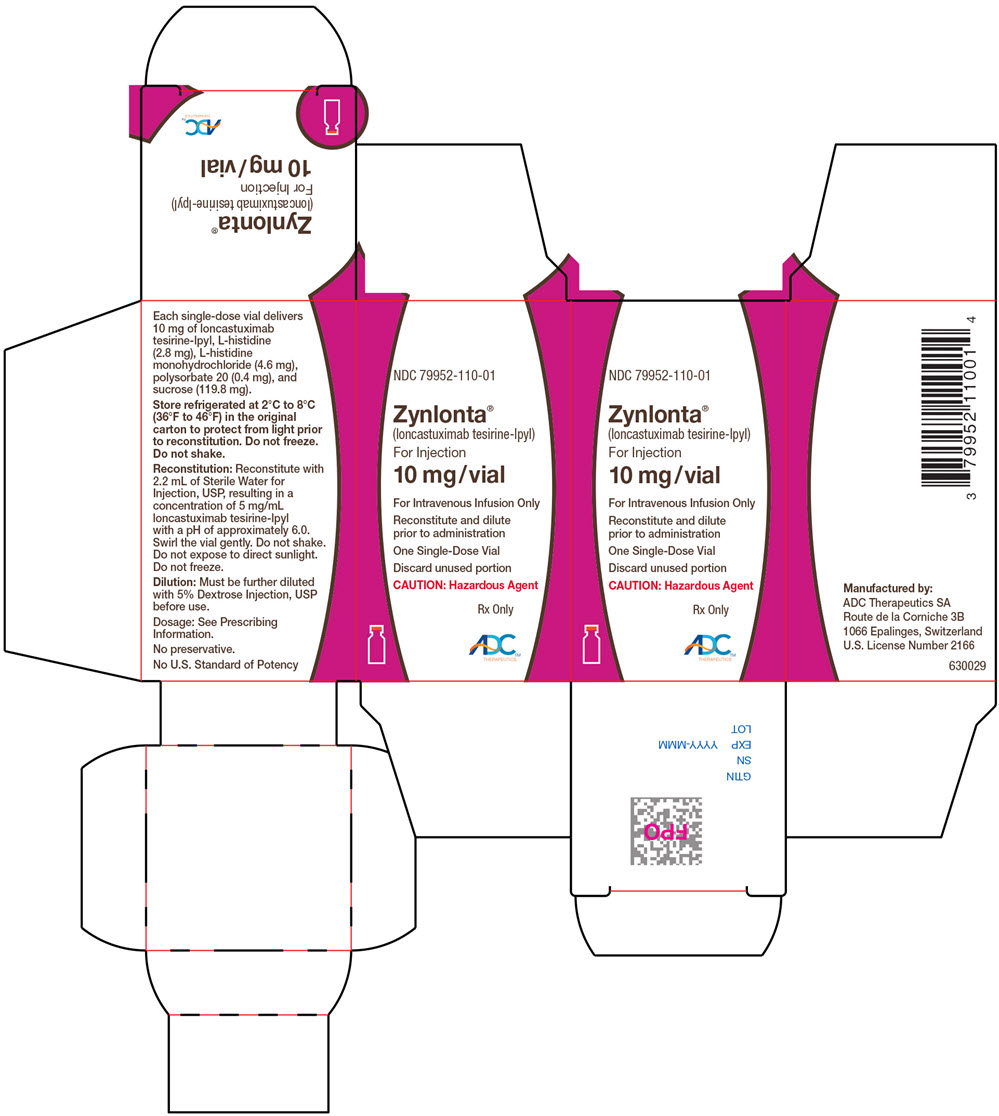 DRUG LABEL: ZYNLONTA
NDC: 79952-110 | Form: INJECTION, POWDER, LYOPHILIZED, FOR SOLUTION
Manufacturer: ADC Therapeutics America, Inc.
Category: prescription | Type: HUMAN PRESCRIPTION DRUG LABEL
Date: 20260226

ACTIVE INGREDIENTS: loncastuximab tesirine 10 mg/2 mL
INACTIVE INGREDIENTS: HISTIDINE; HISTIDINE MONOHYDROCHLORIDE MONOHYDRATE; polysorbate 20; sucrose

HIGHLIGHTS OF PRESCRIBING INFORMATION

These highlights do not include all the information needed to use ZYNLONTA safely and effectively. See full prescribing information for ZYNLONTA.
ZYNLONTA® (loncastuximab tesirine-lpyl) for injection, for intravenous use
Initial U.S. Approval: 2021

RECENT MAJOR CHANGES

Dosage and Administration (2.3) | 2/2026
Warnings and Precautions, Effusion and Edema, Including Capillary Leak Syndrome (5.1) | 2/2026
Warnings and Precautions, Hepatotoxicity, Including Drug-Induced Liver Injury (5.4) | 1/2026

1 INDICATIONS AND USAGE

ZYNLONTA is a CD19-directed antibody and alkylating agent conjugate indicated for the treatment of adult patients with relapsed or refractory large B-cell lymphoma after two or more lines of systemic therapy, including diffuse large B-cell lymphoma (DLBCL) not otherwise specified, DLBCL arising from low-grade lymphoma, and high-grade B-cell lymphoma. (1)

This indication is approved under accelerated approval based on overall response rate. Continued approval for this indication may be contingent upon verification and description of clinical benefit in a confirmatory trial(s). (1)

2 DOSAGE AND ADMINISTRATION

- ZYNLONTA is an intravenous infusion over 30 minutes on Day 1 of each cycle (every 3 weeks). The recommended dosage is:
  - 0.15 mg/kg every 3 weeks for 2 cycles.
  - 0.075 mg/kg every 3 weeks for subsequent cycles. (2.1)
- Premedicate with dexamethasone 4 mg orally or intravenously twice daily for 3 days beginning the day before ZYNLONTA. (2.2)
- See Full Prescribing Information for instructions on preparation and administration. (2.4)

3 DOSAGE FORMS AND STRENGTHS

For injection: 10 mg of loncastuximab tesirine-lpyl as a lyophilized powder in a single-dose vial for reconstitution and further dilution. (3)

4 CONTRAINDICATIONS

None. (4)

5 WARNINGS AND PRECAUTIONS

- Effusion and Edema, Including Capillary Leak Syndrome: Monitor for the development of pleural effusion, pericardial effusion, ascites, peripheral edema, and general edema. Consider diagnostic imaging when symptoms develop or worsen. (5.1)
- Myelosuppression: Monitor blood cell counts. Withhold, reduce, or discontinue ZYNLONTA based on severity. (5.2)
- Infections: Monitor for infection and treat promptly. (5.3)
- Hepatotoxicity, Including Drug-Induced Liver Injury: Monitor liver function tests during treatment. Withhold or permanently discontinue ZYNLONTA based on severity. (5.4)
- Cutaneous Reactions: Monitor patients for new or worsening cutaneous reactions, including photosensitivity reactions. Dermatologic consultation should be considered. (5.5)
- Embryo-Fetal Toxicity: Can cause fetal harm. Advise patients of the potential risk to a fetus and to use effective contraception. (5.6, 8.1, 8.3)

6 ADVERSE REACTIONS

Most common (≥20%) adverse reactions, including laboratory abnormalities, are thrombocytopenia, increased gamma-glutamyltransferase, neutropenia, anemia, hyperglycemia, transaminase elevation, fatigue, hypoalbuminemia, rash, edema, nausea, and musculoskeletal pain. (6.1)

To report SUSPECTED ADVERSE REACTIONS, contact ADC Therapeutics at 1-855-690-0340 or FDA at 1-800-FDA-1088 or www.fda.gov/medwatch.

8 USE IN SPECIFIC POPULATIONS

- Lactation: Advise not to breastfeed. (8.2)
- Severe Hepatic Impairment: Avoid use of ZYNLONTA. (8.6)

FULL PRESCRIBING INFORMATION

1 INDICATIONS AND USAGE

ZYNLONTA is indicated for the treatment of adult patients with relapsed or refractory large B-cell lymphoma after two or more lines of systemic therapy, including diffuse large B-cell lymphoma (DLBCL) not otherwise specified, DLBCL arising from low-grade lymphoma, and high-grade B-cell lymphoma.

This indication is approved under accelerated approval based on overall response rate [see Clinical Studies (14.1)]. Continued approval for this indication may be contingent upon verification and description of clinical benefit in a confirmatory trial(s).

2 DOSAGE AND ADMINISTRATION

2.1 Recommended Dosage

ZYNLONTA as an intravenous infusion administered over 30 minutes on Day 1 of each cycle (every 3 weeks). Administer intravenous infusion as follows:

- 0.15 mg/kg every 3 weeks for 2 cycles.
- 0.075 mg/kg every 3 weeks for subsequent cycles.

2.2 Recommended Premedication

Unless contraindicated, administer dexamethasone 4 mg orally or intravenously twice daily for 3 days beginning the day before administering ZYNLONTA. If dexamethasone administration does not begin the day before ZYNLONTA, dexamethasone should begin at least 2 hours prior to administration of ZYNLONTA.

2.3 Dosage Modifications and Delays

Table 1: Recommended Dosage Modifications for Adverse Reactions
Adverse Reactions | Severity | Dosage Modification
Hematologic Adverse Reactions
Neutropenia [see Warnings and Precautions (5.2)] | Absolute neutrophil count less than 1 × 10^9/L | Withhold ZYNLONTA until neutrophil counts returns to 1 × 10^9/L or higher
Thrombocytopenia [see Warnings and Precautions (5.2)] | Platelet count less than 50,000/mcL | Withhold ZYNLONTA until platelet count returns to 50,000/mcL or higher
Nonhematologic Adverse Reactions
Edema or Effusion [see Warnings and Precautions (5.1)] | Grade 2 [National Cancer Institute Common Terminology Criteria for Adverse Events version 4.0] or higher | Withhold ZYNLONTA until the toxicity resolves to Grade 1 or less
Pericardial Effusion [see Warnings and Precautions (5.1)] | Grade 2 | Withhold ZYNLONTA until the toxicity resolves. Discontinue ZYNLONTA if effusion recurs
 | Grade 3 or higher | Discontinue ZYNLONTA
Hepatotoxicity [see Warnings and Precautions (5.4)] | Grade 3 or higher increase in AST or ALT or suspected DILI | Withhold ZYNLONTA until toxicity resolves to Grade 1 or less, discontinue for confirmed DILI
Other Adverse Reactions [see Warnings and Precautions (5.3), (5.5), Adverse Reactions (6.1)] | Grade 3 or higher | Withhold ZYNLONTA until the toxicity resolves to Grade 1 or less

Recommendations for Dosage Delays

If dosing is delayed by more than 3 weeks due to toxicity related to ZYNLONTA, reduce subsequent doses by 50%. If toxicity reoccurs following dose reduction, consider discontinuation. Note: If toxicity requires dose reduction following the second dose of 0.15 mg/kg (Cycle 2), the patient should receive the dose of 0.075 mg/kg for Cycle 3.

2.4 Reconstitution and Administration Instructions

Reconstitute and further dilute ZYNLONTA prior to intravenous infusion. Use appropriate aseptic technique.

ZYNLONTA is a hazardous drug. Follow applicable special handling and disposal procedures.^1

Dose calculation

Calculate the total dose (mg) required based on the patient's weight and prescribed dose [see Dosage and Administration (2.1)].

- For patients with a body mass index (BMI) ≥35 kg/m^2, calculate the dose based on an adjusted body weight (ABW) as follows:
  ABW in kg = 35 kg/m^2× (height in meters)^2
- More than one vial may be needed to achieve the calculated dose.
- Convert the calculated dose (mg) to volume using 5 mg/mL, which is the concentration of ZYNLONTA after reconstitution.

Reconstitution of lyophilized ZYNLONTA

- Reconstitute each ZYNLONTA vial using 2.2 mL of Sterile Water for Injection, USP with the stream directed toward the inside wall of the vial to obtain a final concentration of 5 mg/mL.
- Swirl the vial gently until the powder is completely dissolved. Do not shake. Do not expose to direct sunlight.
- Inspect the reconstituted solution for particulate matter and discoloration. The solution should appear clear to slightly opalescent, colorless to slightly yellow. Do not use if the reconstituted solution is discolored, is cloudy, or contains visible particulates.
- Use reconstituted ZYNLONTA immediately. If not used immediately, store the reconstituted solution in the vial for up to 4 hours refrigerated at 2°C to 8°C (36°F to 46°F) or room temperature 20°C to 25°C (68°F to 77°F). Do not freeze.
- The product does not contain a preservative. Discard unused vial after reconstitution if the recommended storage time is exceeded.

Dilution in infusion bag

- Withdraw the required volume of reconstituted solution from the ZYNLONTA vial using a sterile syringe. Discard any unused portion left in the vial.
- Add the calculated dose volume of ZYNLONTA solution into a 50 mL infusion bag of 5% Dextrose Injection, USP.
- Gently mix the intravenous bag by slowly inverting the bag. Do not shake.
- If not used immediately, store the diluted ZYNLONTA infusion solution refrigerated at 2°C to 8°C (36°F to 46°F) for up to 24 hours or at room temperature 20°C to 25°C (68°F to 77°F) for up to 8 hours. Discard diluted infusion bag if storage time exceeds these limits. Do not freeze.
- No incompatibilities have been observed between ZYNLONTA and intravenous infusion bags with product-contacting materials of polyvinylchloride (PVC), polyolefin (PO), and PAB® (copolymer of ethylene and propylene).

Administration

- Administer by intravenous infusion over 30 minutes using a dedicated infusion line equipped with a sterile, non-pyrogenic, low-protein binding in-line or add-on filter (0.2- or 0.22-micron pore size) and catheter.
- Extravasation of ZYNLONTA has been associated with irritation, swelling, pain, and/or tissue damage, which may be severe [see Adverse Reactions (6.1)]. Monitor the infusion site for possible subcutaneous infiltration during drug administration.
- Do not mix ZYNLONTA with or administer as an infusion with other drugs.

3 DOSAGE FORMS AND STRENGTHS

For Injection: 10 mg of loncastuximab tesirine-lpyl as a white to off-white lyophilized powder in a single-dose vial for reconstitution and further dilution.

4 CONTRAINDICATIONS

None.

5 WARNINGS AND PRECAUTIONS

5.1 Effusion and Edema, Including Capillary Leak Syndrome

Serious effusion and edema, including capillary leak syndrome, occurred in patients treated with ZYNLONTA. Grade 3 edema occurred in 3% (primarily peripheral edema or ascites) and Grade 3 pleural effusion occurred in 3%, and Grade 3 or 4 pericardial effusion occurred in 1% [see Adverse Reactions (6.1)]. Rare cases of cardiac tamponade have been reported in patients with Grade 3 or 4 pericardial effusion. Grade 3 or higher capillary leak syndrome occurred in 0.6%.

Monitor patients for new or worsening edema or effusions. Consider diagnostic imaging in patients who develop symptoms of pleural effusion or pericardial effusion, such as new or worsened dyspnea, chest pain, and/or ascites such as swelling in the abdomen and bloating. Institute appropriate medical management for edema or effusions.

Evaluate and institute appropriate medical management for capillary leak syndrome in patients experiencing worsening effusion or edema, with signs and symptoms of weight gain, severe hypotension, hypoalbuminemia, and/or hemoconcentration (by elevated hemoglobin/hematocrit, etc.).

Withhold or discontinue ZYNLONTA based on severity [see Dosage and Administration (2.3)].

5.2 Myelosuppression

Treatment with ZYNLONTA can cause serious or severe myelosuppression, including neutropenia, thrombocytopenia, and anemia. Grade 3 or 4 neutropenia occurred in 32%, thrombocytopenia in 20%, and anemia in 12% of patients. Grade 4 neutropenia occurred in 21% and thrombocytopenia in 7% of patients. Febrile neutropenia occurred in 3% [see Adverse Reactions (6.1)].

Monitor complete blood counts throughout treatment. Cytopenias may require interruption, dose reduction, or discontinuation of ZYNLONTA. Consider prophylactic granulocyte colony-stimulating factor administration as applicable [see Dosage and Administration (2.3)].

5.3 Infections

Fatal and serious infections, including opportunistic infections, occurred in patients treated with ZYNLONTA. Grade 3 or higher infections occurred in 10% of patients, with fatal infections occurring in 2%. The most frequent Grade ≥3 infections included sepsis and pneumonia [see Adverse Reactions (6.1)].

Monitor for any new or worsening signs or symptoms consistent with infection. For Grade 3 or 4 infection, withhold ZYNLONTA until infection has resolved [see Dosage and Administration (2.3)].

5.4 Hepatotoxicity, Including Drug-Induced Liver Injury

Cholestatic and hepatocellular liver injury, including severe, life-threatening, and fatal cases of drug-induced liver injury (DILI), have occurred in patients treated with ZYNLONTA.

Monitor liver function tests at baseline and throughout treatment with ZYNLONTA. In the event of suspected DILI or Grade ≥3 increase in ALT or AST, withhold ZYNLONTA until toxicity resolves to Grade 1 or lower. Upon confirmation of DILI, discontinue ZYNLONTA. [see Dosage and Administration (2.3)].

ZYNLONTA should be avoided in patients with severe hepatic impairment [see Clinical Pharmacology (8.6, 12.3)].

5.5 Cutaneous Reactions

Serious cutaneous reactions occurred in patients treated with ZYNLONTA. Grade 3 cutaneous reactions occurred in 4% and included photosensitivity reaction, rash (including exfoliative and maculo-papular), and erythema [see Adverse Reactions (6.1)].

Monitor patients for new or worsening cutaneous reactions, including photosensitivity reactions. Withhold ZYNLONTA for severe (Grade 3) cutaneous reactions until resolution [see Dosage and Administration (2.3)]. Advise patients to minimize or avoid exposure to direct natural or artificial sunlight including exposure through glass windows. Instruct patients to protect skin from exposure to sunlight by wearing sun-protective clothing and/or the use of sunscreen products. If a skin reaction or rash develops, dermatologic consultation should be considered [see Nonclinical Toxicology (13)].

5.6 Embryo-Fetal Toxicity

Based on its mechanism of action, ZYNLONTA can cause embryo-fetal harm when administered to a pregnant woman because it contains a genotoxic compound (SG3199) and affects actively dividing cells.

Advise pregnant women of the potential risk to a fetus. Advise females of reproductive potential to use effective contraception during treatment with ZYNLONTA and for 10 months after the last dose. Advise male patients with female partners of reproductive potential to use effective contraception during treatment with ZYNLONTA, and for 7 months after the last dose [see Use in Specific Populations (8.1, 8.3)].

6 ADVERSE REACTIONS

The following clinically significant adverse reactions are described elsewhere in the labeling:

Effusion and Edema [see Warnings and Precautions (5.1)]

Myelosuppression [see Warnings and Precautions (5.2)]

Infections [see Warnings and Precautions (5.3)]

Hepatotoxicity, including DILI [see Warnings and Precautions(5.4)]

Cutaneous Reactions [see Warnings and Precautions (5.5)]

6.1 Clinical Trials Experience

Because clinical trials are conducted under widely varying conditions, adverse reaction rates observed in the clinical trials of a drug cannot be directly compared to rates in the clinical trials of another drug and may not reflect the rates observed in practice.

The pooled safety population described in the WARNINGS AND PRECAUTIONS reflect exposure to ZYNLONTA as a single agent at an initial dose of 0.15 mg/kg in 215 patients with DLBCL in studies ADCT-402-201 (LOTIS-2) and ADCT-402-101, which includes 145 patients from LOTIS-2 treated with 0.15 mg/kg × 2 cycles followed by 0.075 mg/kg for subsequent cycles. Among 215 patients who received ZYNLONTA, the median number of cycles was 3 (range 1 to 15) with 58% receiving three or more cycles and 30% receiving five or more cycles.

In this pooled safety population of 215 patients, the most common (>20%) adverse reactions, including laboratory abnormalities, were thrombocytopenia, increased gamma-glutamyltransferase, neutropenia, anemia, hyperglycemia, transaminase elevation, fatigue, hypoalbuminemia, rash, edema, nausea, and musculoskeletal pain.

Relapsed or Refractory Diffuse Large B-Cell Lymphoma

LOTIS-2

The safety of ZYNLONTA was evaluated in LOTIS-2, an open-label, single-arm clinical trial that enrolled 145 patients with relapsed or refractory diffuse large B-cell lymphoma (DLBCL), including high-grade B-cell lymphoma, after at least two prior systemic therapies [see Clinical Studies (14.1)]. The trial required hepatic transaminases, including gamma-glutamyltransferase (GGT), ≤2.5 times upper limit of normal (ULN), total bilirubin ≤1.5 times ULN, and creatinine clearance ≥60 mL/min. Patients received ZYNLONTA 0.15 mg/kg every 3 weeks for 2 cycles, then 0.075 mg/kg every 3 weeks for subsequent cycles and received treatment until progressive disease or unacceptable toxicity. Among the 145 patients, the median number of cycles received was 3, with 34% receiving 5 or more cycles.

The median age was 66 years (range 23 to 94), 59% were male, and 94% had an Eastern Cooperative Oncology Group (ECOG) performance status of 0 to 1. Race was reported in 97% of patients; of these patients, 90% were White, 3% were Black, and 2% were Asian.

Serious adverse reactions occurred in 28% of patients receiving ZYNLONTA. The most common serious adverse reactions that occurred in ≥2% receiving ZYNLONTA were febrile neutropenia, pneumonia, edema, pleural effusion, and sepsis. Fatal adverse reactions occurred in 1%, due to infection.

Permanent treatment discontinuation due to an adverse reaction of ZYNLONTA occurred in 19% of patients. Adverse reactions resulting in permanent discontinuation of ZYNLONTA in ≥2% were gamma-glutamyltransferase increased, edema, and effusion.

Dose reductions due to an adverse reaction of ZYNLONTA occurred in 8% of patients. Adverse reactions resulting in dose reduction of ZYNLONTA in ≥4% was gamma-glutamyltransferase increased.

Dosage interruptions due to an adverse reaction occurred in 49% of patients receiving ZYNLONTA. Adverse reactions leading to interruption of ZYNLONTA in ≥5% were gamma-glutamyltransferase increased, neutropenia, thrombocytopenia, and edema.

Table 2 summarizes the adverse reactions in LOTIS-2.

Table 2: Adverse Reactions (≥10%) in Patients with Relapsed or Refractory DLBCL who received ZYNLONTA in LOTIS-2
Adverse Reaction | ZYNLONTA (N=145)
Adverse Reaction | All Grades (%) | Grades 3 or 4 (%)
General Disorders and Administration Site Conditions
Fatigue [Fatigue includes fatigue, asthenia, and lethargy] | 38 | 1 [No Grade 4 adverse reactions occurred]
Edema [Edema includes edema, face edema, generalized edema, peripheral edema, ascites, fluid overload, peripheral swelling, swelling, and swelling face] | 28 | 3
Skin and Subcutaneous Tissue Disorders
Rash [Rash includes rash, rash erythematous, rash maculopapular, rash pruritic, rash pustular, erythema, generalized erythema, dermatitis, dermatitis acneiform, dermatitis bullous, dermatitis exfoliative generalized, and palmar-plantar erythrodysesthesia syndrome] | 30 | 2
Pruritus | 12 | 0
Photosensitivity reaction | 10 | 2
Gastrointestinal Disorders
Nausea | 23 | 0
Diarrhea | 17 | 2
Abdominal pain [Abdominal pain includes abdominal pain, abdominal discomfort, abdominal pain lower, and abdominal pain upper] | 14 | 3
Vomiting | 13 | 0
Constipation | 12 | 0
Musculoskeletal and Connective Tissue Disorders
Musculoskeletal pain [Musculoskeletal pain includes musculoskeletal pain, musculoskeletal chest pain, musculoskeletal discomfort, back pain, limb discomfort, myalgia, neck pain, non-cardiac chest pain, and pain in extremity] | 23 | 1
Metabolism and Nutrition Disorders
Decreased appetite | 15 | 0
Respiratory Disorders
Dyspnea [Dyspnea includes dyspnea, and dyspnea exertional] | 13 | 1
Pleural effusion | 10 | 2
Infection
Upper respiratory tract infection [Upper respiratory tract infection includes upper respiratory tract infection, upper respiratory tract congestion, nasopharyngitis, rhinitis, rhinovirus infection, and sinusitis] | 10 | <1

Clinically relevant adverse reactions in <10% of patients (all grades) who received ZYNLONTA included:

- Blood and lymphatic system disorders: Febrile neutropenia (3%)
- Cardiac disorders: Pericardial effusion (3%)
- Infections: Pneumonia [Pneumonia includes pneumonia and lung infection] (5%), sepsis [Sepsis includes sepsis, escherichia sepsis, and septic shock] (2%)
- Skin and subcutaneous disorders: Hyperpigmentation (4%)
- General disorders: Infusion site extravasation (<1%)

Selected Other Adverse Reactions

- Inflammatory-related conditions were reported in 3% of patients in LOTIS-2, including pericarditis, pneumonitis, pleuritis, and dermatitis.

Table 3 summarizes the laboratory abnormalities in LOTIS-2.

Table 3: Select Laboratory Abnormalities (≥10%) That Worsened from Baseline in Patients with Relapsed or Refractory DLBCL Who Received ZYNLONTA in LOTIS-2
Laboratory Abnormality | ZYNLONTA [The denominator used to calculate the rate varied from 143 to 145 based on the number of patients with a baseline value and at least one post-treatment value]
Laboratory Abnormality | All Grades (%) | Grade 3 or 4 (%)
Hematologic
Platelets decreased | 58 | 17
Neutrophils decreased | 52 | 30
Hemoglobin decreased | 51 | 10 [No Grade 4 adverse reactions occurred]
Chemistry
GGT increased | 57 | 21
Glucose increased | 48 | 8
AST increased | 41 | <1
Albumin decreased | 37 | <1
ALT increased | 34 | 3

Other Clinical Trials Experience

The following adverse reactions have been reported following administration of ZYNLONTA:

- Hepatotoxicity, including drug- induced liver injury (DILI).

6.2 Postmarketing Experience

The following adverse reactions have been identified during postapproval use of ZYNLONTA. Because these reactions are reported voluntarily from a population of uncertain size, it is not always possible to reliably estimate their frequency or establish a causal relationship to drug exposure.

Skin and Subcutaneous Tissue Disorders: Telangiectasia, including cutaneous collagenous vasculopathy, blister, rash vesicular.

8 USE IN SPECIFIC POPULATIONS

8.1 Pregnancy

Risk Summary

Based on its mechanism of action, ZYNLONTA can cause embryo-fetal harm when administered to a pregnant woman, because it contains a genotoxic compound (SG3199) and affects actively dividing cells [see Clinical Pharmacology (12.1) and Nonclinical Toxicology (13.1)]. There are no available data on the use of ZYNLONTA in pregnant women to evaluate for drug-associated risk. No animal reproduction studies were conducted with ZYNLONTA. Advise pregnant women of the potential risk to a fetus.

The estimated background risk of major birth defects and miscarriage for the indicated population is unknown. All pregnancies have a background risk of birth defect, loss, or other adverse outcomes. In the U.S. general population, the estimated background risk of major birth defects and miscarriage in clinically recognized pregnancies is 2-4% and 15-20%, respectively.

Data

Animal Data

Animal reproductive or developmental toxicity studies were not conducted with loncastuximab tesirine-lpyl. The cytotoxic component of ZYNLONTA, SG3199, crosslinks DNA, is genotoxic, and is toxic to rapidly dividing cells, suggesting it has the potential to cause embryotoxicity and teratogenicity.

8.2 Lactation

Risk Summary

There is no data on the presence of loncastuximab tesirine-lpyl or SG3199 in human milk, the effects on the breastfed child, or milk production. Because of the potential for serious adverse reactions in breastfed children, advise women not to breastfeed during treatment with ZYNLONTA and for 3 months after the last dose.

8.3 Females and Males of Reproductive Potential

ZYNLONTA can cause fetal harm when administered to pregnant women [see Use in Specific Populations (8.1)].

Pregnancy Testing

Pregnancy testing is recommended for females of reproductive potential prior to initiating ZYNLONTA.

Contraception

Females

Advise women of reproductive potential to use effective contraception during treatment and for 10 months after the last dose.

Males

Because of the potential for genotoxicity, advise males with female partners of reproductive potential to use effective contraception during the treatment with ZYNLONTA and for 7 months after the last dose [see Nonclinical Toxicology (13.1)].

Infertility

Males

Based on the results from animal studies, ZYNLONTA may impair fertility in males. The effects were not reversible in male cynomolgus monkeys during the 12-week drug-free period [see Nonclinical Toxicology (13.1)].

8.4 Pediatric Use

Safety and effectiveness of ZYNLONTA in pediatric patients have not been established.

8.5 Geriatric Use

Of the 145 patients with large B-cell lymphoma who received ZYNLONTA in clinical trials, 55% were 65 years of age and older, while 14% were 75 years of age and older [see Clinical Studies (14.1)]. No overall differences in safety or effectiveness were observed between these patients and younger patients.

8.6 Hepatic Impairment

No dose adjustment is recommended for patients with mild hepatic impairment (total bilirubin ≤ upper limit of normal [ULN] and aspartate aminotransferase (AST) > ULN or total bilirubin > 1 to 1.5 × ULN and any AST). Monitor patients with mild hepatic impairment for potential increased incidence of adverse reactions and modify the ZYNLONTA dosage in the event of adverse reactions [see Dosage and Administration (2.3)].

There is limited safety information available in patients with moderate hepatic impairment. ZYNLONTA should be avoided in patients with severe hepatic impairment [see Clinical Pharmacology (12.3)].

11 DESCRIPTION

Loncastuximab tesirine-lpyl is a CD19-directed antibody and alkylating agent conjugate, consisting of a humanized IgG1 kappa monoclonal antibody conjugated to SG3199, a pyrrolobenzodiazepine (PBD) dimer cytotoxic alkylating agent, through a protease-cleavable valine-alanine linker. SG3199 attached to the linker is designated as SG3249, also known as tesirine.

Loncastuximab tesirine-lpyl has an approximate molecular weight of 151 kDa. An average of 2.3 molecules of SG3249 are attached to each antibody molecule. Loncastuximab tesirine-lpyl is produced by chemical conjugation of the antibody and small molecule components. The antibody is produced by mammalian (Chinese hamster ovary) cells, and the small molecule components are produced by chemical synthesis.

ZYNLONTA (loncastuximab tesirine-lpyl) for injection is supplied as a sterile, white to off-white, preservative-free, lyophilized powder, which has a cake-like appearance, for intravenous infusion after reconstitution and dilution. Each single-dose vial delivers 10 mg of loncastuximab tesirine-lpyl, L-histidine (2.8 mg), L-histidine monohydrochloride (4.6 mg), polysorbate 20 (0.4 mg), and sucrose (119.8 mg). After reconstitution with 2.2 mL Sterile Water for Injection, USP, the final concentration is 5 mg/mL with a pH of approximately 6.0.

12 CLINICAL PHARMACOLOGY

12.1 Mechanism of Action

Loncastuximab tesirine-lpyl is an antibody-drug conjugate (ADC) targeting CD19. The monoclonal IgG1 kappa antibody component binds to human CD19, a transmembrane protein expressed on the surface of cells of B-lineage origin. The small molecule component is SG3199, a PBD dimer and alkylating agent.

Upon binding to CD19, loncastuximab tesirine-lpyl is internalized followed by release of SG3199 via proteolytic cleavage. The released SG3199 binds to the DNA minor groove and forms highly cytotoxic DNA interstrand crosslinks, subsequently inducing cell death. Loncastuximab tesirine-lpyl had anticancer activity in animal models of lymphoma.

12.2 Pharmacodynamics

Higher loncastuximab tesirine-lpyl exposure in Cycle 1 was associated with higher incidence of some Grade ≥2 adverse reactions, including skin and nail reactions, liver function test abnormalities and increased gamma-glutamyltransferase. Lower loncastuximab tesirine-lpyl exposure in Cycle 1 was associated with lower efficacy over the dose range of 0.015-0.2 mg/kg (0.1 to 1.33 times the maximum recommended dose).

Cardiac Electrophysiology

At the maximum recommended therapeutic dose of 0.15 mg/kg during Cycle 1 and Cycle 2, loncastuximab tesirine-lpyl does not cause large mean increases (i.e., >20 msec) in the QTc interval.

12.3 Pharmacokinetics

The exposure of loncastuximab tesirine-lpyl at the approved recommended dosage in Cycle 2 and at steady state is shown in Table 4. Loncastuximab tesirine-lpyl steady state Cmax was 28.2% lower than the Cmax after the first dose. The time to reach steady state was 105 days.

Table 4: Loncastuximab Tesirine-lpyl Exposure Parameters [Data presented as mean and coefficient of variation (CV %)]
Time | Cmax (ng/mL) | AUCtau (ng ∙ day/mL)
Cycle 2 | 2,911 (35.3%) | 21,665 (54.1%)
Steady state | 1,776 (32.1%) | 16,882 (38.2%)
Cmax = Maximum observed serum concentration; AUCtau = Area under curve over the dosing interval

Distribution

The mean (CV%) of loncastuximab tesirine-lpyl volume of distribution was 7.11 (26.6%) L.

Elimination

The mean (CV%) of loncastuximab tesirine-lpyl clearance decreased with time from 0.499 L/day (89.3%) after a single dose to 0.275 L/day (38.2%) at steady state. The mean (standard deviation) half-life of loncastuximab tesirine-lpyl was 20.8 (7.06) days at steady state.

Metabolism

The monoclonal antibody portion of loncastuximab tesirine-lpyl is expected to be metabolized into small peptides by catabolic pathways. The small molecule cytotoxin, SG3199, is metabolized by CYP3A4/5 in vitro.

Excretion

The major excretion pathways of SG3199 have not been studied in humans. SG3199 is expected to be minimally renally excreted.

Specific Populations

No clinically significant differences in the pharmacokinetics of loncastuximab tesirine-lpyl were observed based on age (20-94 years), sex, race (White vs. Black), body weight (42.1 to 160.5 kg), ECOG status (0 to 2) or mild to moderate renal impairment (CLcr 30 to <90 mL/min using the Cockcroft-Gault equation).

The effect of severe renal impairment (CLcr 15 to 29 mL/min), and end-stage renal disease with or without hemodialysis on loncastuximab tesirine-lpyl pharmacokinetics is unknown.

Patients with Hepatic Impairment

Mild hepatic impairment (total bilirubin ≤ ULN and AST > ULN, or total bilirubin >1 to 1.5 × ULN and any AST) may increase the exposure of unconjugated SG3199, however there was no clinically significant effect on loncastuximab tesirine-lpyl pharmacokinetics. There is insufficient data in patients with moderate (total bilirubin >1.5 to ≤3 × ULN and any AST) hepatic impairment or severe (total bilirubin >3 ULN and any AST) hepatic impairment.

Drug Interaction Studies

In Vitro Studies

Cytochrome P450 (CYP) Enzymes: SG3199 does not inhibit CYP1A2, CYP2A6, CYP2B6, CYP2C8, CYP2C9, CYP2C19, CYP2D6, CYP2E1, or CYP3A4/5 at clinically relevant unconjugated SG3199 concentrations.

Transporter Systems: SG3199 is a substrate of P-glycoprotein (P-gp), but not a substrate of breast cancer resistance protein (BCRP), organic anion-transporting polypeptide (OATP)1B1, or organic cation transporter (OCT)1.

SG3199 does not inhibit P-gp, BCRP, OATP1B1, OATP1B3, organic anion transporter (OAT)1, OAT3, OCT2, OCT1, multi-antimicrobial extrusion protein (MATE)1, MATE2-K, or bile salt export pump (BSEP) at clinically relevant unconjugated SG3199 concentrations.

12.6 Immunogenicity

As with all therapeutic proteins, there is potential for immunogenicity. The detection of antibody formation is highly dependent on the sensitivity and specificity of the assay. Additionally, the observed incidence of antibody (including neutralizing antibody) positivity in an assay may be influenced by several factors including assay methodology, sample handling, timing of sample collection, concomitant medications, and underlying disease. For these reasons, comparison of the incidence of antibodies in the studies described below with the incidence of antibodies to loncastuximab tesirine-lpyl in other studies or to other products may be misleading.

In LOTIS-2, 0 of 134 patients tested positive for antibodies against loncastuximab tesirine-lpyl after treatment. The potential effect of anti-drug antibodies to ZYNLONTA on pharmacokinetics, efficacy, or safety is unknown.

13 NONCLINICAL TOXICOLOGY

13.1 Carcinogenesis, Mutagenesis, Impairment of Fertility

Carcinogenicity studies have not been conducted with loncastuximab tesirine-lpyl or SG3199.

SG3199 was genotoxic in an in vitro micronucleus test and a chromosome aberration assay using human lymphocytes through a clastogenic mechanism. These results are consistent with the pharmacological effect of SG3199 as a covalent DNA crosslinking agent. Results of a bacterial reverse mutation assay (Ames test) were inconclusive due to cytotoxicity.

Fertility studies have not been conducted with loncastuximab tesirine-lpyl. Results from repeat- dose toxicity studies with intravenous administration of loncastuximab tesirine-lpyl in cynomolgus monkeys indicate the potential for impaired male reproductive function and fertility. Administration of loncastuximab tesirine-lpyl to cynomolgus monkeys every 3 weeks at 0.6 mg/kg for a total of 2 doses, or every 3 weeks at 0.3 mg/kg for 13 weeks resulted in adverse findings that included decreased weight and/or size of the testes and epididymis, atrophy of the seminiferous tubules, germ cell degeneration, and/or reduced sperm content. The dose of 0.3 mg/kg in animals results in an exposure (AUC) that is approximately 3 times the exposure at the maximum recommended human dose [MRHD] of 0.15 mg/kg. Findings were not reversible at the end of the 12-week recovery period following 4 or 13 weeks of dosing.

13.2 Animal Toxicology and/or Pharmacology

Inflammatory-mediated toxicities associated with PBDs have been observed at low incidence in animals. In repeat-dose toxicity studies in cynomolgus monkeys, administration of loncastuximab tesirine-lpyl was associated with potential inflammatory mediated-toxicities, including in the lungs and kidneys. Renal toxicity including increased kidney weights and nephropathy with variable inflammation and fibrosis that was reversible was observed in monkeys. Black skin spots potentially related to phototoxicity were observed and were still present after the 12-week treatment-free period.

14 CLINICAL STUDIES

14.1 Relapsed or Refractory Diffuse Large B-cell Lymphoma

The efficacy of ZYNLONTA was evaluated in LOTIS-2 (NCT03589469), an open-label, single- arm trial in 145 adult patients with relapsed or refractory diffuse large B-cell lymphoma (DLBCL) after at least 2 prior systemic regimens. The trial excluded patients with bulky disease and active central nervous system lymphoma. Patients received ZYNLONTA 0.15 mg/kg every 3 weeks for 2 cycles, then 0.075 mg/kg every 3 weeks for subsequent cycles and received treatment until progressive disease, or unacceptable toxicity.

Of the 145 patients enrolled, the median age was 66 years (range 23 to 94), 59% male, and 94% had an ECOG performance status of 0 to 1. Race was reported in 97% of patients; of these patients, 90% were White, 3% were Black, and 2% were Asian. The diagnosis was DLBCL not otherwise specified (NOS) in 88% (including 20% with DLBCL arising from low-grade lymphoma) and high-grade B-cell lymphoma in 7%. The median number of prior therapies was 3 (range 2 to 7), 63% with refractory disease, 17% with prior stem cell transplant, and 9% with prior chimeric antigen receptor (CAR) T-cell therapy.

Efficacy was established on the basis of overall response rate (ORR) as assessed by an Independent Review Committee (IRC) using Lugano 2014 criteria (Table 5). The median follow- up time was 7.3 months (range 0.3 to 20.2).

Table 5 Efficacy Results in Patients with Relapsed or Refractory DLBCL
Efficacy Parameter | ZYNLONTA N = 145
Overall response rate by IRC [IRC = independent review committee using Lugano 2014 criteria] , (95% CI) | 48.3% (39.9, 56.7)
Complete response rate (95% CI) | 24.1% (17.4, 31.9)
Partial response rate (95% CI) | 24.1% (17.4, 31.9)
Duration of overall response [Of 70 patients with objective response, 25 (36%) were censored prior to 3 months. Twenty- six percent of responders had a duration of response ≥6 months] | N = 70
Median (95% CI), months | 10.3 (6.9, NE)
CI = confidence interval, NE = not estimable

The median time to response was 1.3 months (range 1.1 to 8.1).

15 REFERENCES

1. "OSHA Hazardous Drugs." OSHA. http://www.osha.gov/SLTC/hazardousdrugs/index.html

16 HOW SUPPLIED/STORAGE AND HANDLING

How Supplied

ZYNLONTA (loncastuximab tesirine-lpyl) for injection is a sterile, preservative-free, white to off-white lyophilized powder, which has a cake-like appearance, supplied in a single-dose vial for reconstitution and further dilution. Each carton (NDC 79952-110-01) contains one 10 mg single-dose vial.

Storage and Handling

Store refrigerated at 2°C to 8°C (36°F to 46°F) in original carton to protect from light. Do not use beyond the expiration date shown on the carton. Do not freeze. Do not shake.

Special Handling

ZYNLONTA is a hazardous drug. Follow applicable special handling and disposal procedures.^1

Any unused drug product or waste material should be disposed in accordance with local requirements.

17 PATIENT COUNSELING INFORMATION

Advise the patient to read the FDA-approved patient labeling (Patient Information).

- Effusion and Edema, Including Capillary Leak Syndrome: Advise patients to contact their healthcare provider if they experience swelling, rapid weight gain, shortness of breath, worsening malaise, dizziness, or difficult, labored breathing. [see Warnings and Precautions (5.1)].
- Myelosuppression: Advise patients to immediately contact their healthcare provider for a fever of 100.4°F (38°C) or greater, or signs or symptoms of bruising or bleeding. Advise patients of the need for periodic monitoring of blood counts [see Warnings and Precautions (5.2)].
- Infections: Advise patients to immediately contact their healthcare provider for signs or symptoms of infection, including fever, chills, weakness and/or difficulty breathing [see Warnings and Precautions (5.3)].
- Hepatotoxicity, Including Drug-Induced Liver Injury: Inform patients that liver problems, including drug-induced liver injury and abnormalities in liver tests, may develop during ZYNLONTA treatment. Advise patients that they will need monitoring of their liver through regular blood testing throughout their treatment. Advise patients to contact their healthcare provider immediately if they experience abdominal discomfort, pruritus, dark urine, or jaundice. [see Warnings and Precautions (5.4)].
- Cutaneous Reactions: Advise patients that skin reaction or rash can occur. Patients should be directed to minimize or avoid exposure to direct natural or artificial sunlight, including sunlight exposure through glass windows. Patients should be instructed to protect skin from exposure to sunlight by wearing sun-protective clothing and/or the use of sunscreen products [see Warnings and Precautions (5.5)].
- Embryo-Fetal Toxicity:
  - Advise pregnant women of the potential risk to a fetus. Advise female patients of reproductive potential to contact their healthcare provider if they become pregnant, or if pregnancy is suspected, during treatment with ZYNLONTA [see Use in Specific Populations (8.1)].
  - Advise women of reproductive potential to use effective contraception during treatment with ZYNLONTA and for 10 months after the last dose.
  - Advise male patients with female partners of reproductive potential, to use effective contraception during treatment with ZYNLONTA and for 7 months after the last dose [see Warnings and Precautions (5.6) and Use in Specific Populations (8.1), (8.3)].

- Lactation: Advise women not to breastfeed during treatment with ZYNLONTA and for 3 months after the last dose [see Use in Specific Populations (8.2)].

Manufactured by:
ADC Therapeutics SA
Route de la Corniche 3B
1066 Epalinges, Switzerland
U.S. license No. 2166

Distributed by:
ADC Therapeutics America
Murray Hill, New Jersey 07974

For more information, go to www.ZYNLONTA.com or call 1-855-690-0340

ZYNLONTA is a registered trademark of ADC Therapeutics SA

PAB is a registered trademark of B. Braun Medical Inc.

PATIENT INFORMATION
ZYNLONTA® (zin lon' tah)
(loncastuximab tesirine-lpyl)
for injection, for intravenous use

What is ZYNLONTA?
ZYNLONTA is a prescription medicine used to treat adults with certain types of large B-cell lymphoma that has come back (relapsed) or that did not respond to previous treatment (refractory), who have already received 2 or more treatments for their cancer.
It is not known if ZYNLONTA is safe and effective in children.

Before you receive ZYNLONTA, tell your healthcare provider about all of your medical conditions, including if you:

- have an active infection or have had an infection recently.
- have liver problems.
- are pregnant or plan to become pregnant. ZYNLONTA can harm your unborn baby.
  Females who can become pregnant:
  - Your healthcare provider may do a pregnancy test before starting treatment with ZYNLONTA.
  - You should use effective birth control (contraception) during treatment with ZYNLONTA and for 10 months after the last dose of ZYNLONTA. Talk to your healthcare provider about effective birth control. Tell your healthcare provider right away if you become pregnant or think that you are pregnant during treatment with ZYNLONTA.
  Males with female partners who can become pregnant:
  - You should use effective birth control (contraception) during treatment with ZYNLONTA and for 7 months after the last dose of ZYNLONTA.
- are breastfeeding or plan to breastfeed. It is not known if ZYNLONTA passes into breast milk. Do not breastfeed during treatment with ZYNLONTA and for 3 months after the last dose of ZYNLONTA.

Tell your healthcare provider about all the medicines that you take, including prescription and over-the-counter medicines, vitamins, and herbal supplements. Know the medicines you take. Keep a list of them to show your healthcare provider or pharmacist when you get new medicine.

How will I receive ZYNLONTA?

- ZYNLONTA is given to you by your healthcare provider as an intravenous (IV) infusion into your vein over 30 minutes.
- ZYNLONTA is usually given every 3 weeks.
- Your healthcare provider may give you medicine before each infusion to decrease your chance of side effects.
- Your healthcare provider should do blood tests regularly to check for side effects of ZYNLONTA.
- Your healthcare provider will decide how many treatments you need.

What should I avoid while receiving ZYNLONTA?
Avoid or limit your exposure to sunlight, including sunlight through glass, such as buildings or vehicle windows and artificial sunlight such as sunlamps or tanning beds. Exposure to sunlight during treatment with ZYNLONTA can cause skin reaction or rash. Use sun protection measures such as sunscreen and wear loose-fitting clothes that cover your skin while out in sunlight.

What are the possible side effects of ZYNLONTA?
ZYNLONTA may cause serious side effects, including:

- Fluid retention, including capillary leak syndrome (CLS). Fluid retention has happened in people treated with ZYNLONTA, and can be serious and become life-threatening. Too much fluid buildup in your body can cause fluid to leak from blood vessels into the body's tissues. This condition is called capillary leak syndrome (CLS). Tell your healthcare provider and get emergency help right away if you develop new or worsening signs and symptoms of fluid retention including CLS:

- swelling or puffiness
- rapid weight gain
- chest pain
- trouble breathing

- feeling unusually weak or tired
- dizziness or feeling faint especially when standing up

- Low blood cell counts (platelets, red blood cells, and white blood cells). Low blood cell counts are common with ZYNLONTA but can also be serious or severe. Your healthcare provider will monitor your blood counts during treatment with ZYNLONTA. Tell your healthcare provider right away if you get a fever of 100.4°F (38°C) or above, or any bruising or bleeding.
- Infections. Serious infections, including infections that can cause death, have happened in people treated with ZYNLONTA. Tell your healthcare provider right away if you get new or worsening signs or symptoms of infection, including:

- fever
- chills
- flu-like symptoms (cough, tiredness or and body aches)

- headache
- breathing problems
- cuts or scrapes that are red, warm, weakness, swollen or painful

- Liver problems, including Drug-Induced Liver Injury (DILI). Liver problems have happened in people treated with ZYNLONTA, and can be severe or life-threatening, or cause death. Your healthcare provider will do blood tests to monitor your liver function before and during treatment with ZYNLONTA. Tell your healthcare provider if you get stomach-area (abdomen) discomfort, itching of the skin, dark or "tea-colored" urine, or yellowing of your skin or the whites of your eyes (jaundice).
- Skin reactions. Serious skin reactions have happened in people treated with ZYNLONTA. Tell your healthcare provider if you get new or worsening skin reactions, including sensitivity to sunlight, skin rash, peeling, redness or irritation. You may burn more easily or get severe sunburns. See "What should I avoid while receiving ZYNLONTA?"

Your healthcare provider may temporarily stop your treatment, lower your dose or permanently stop treatment with ZYNLONTA if you have certain severe side effects.

The most common side effects of ZYNLONTA include:

- feeling tired or weak
- skin rash
- swelling
- nausea

- muscle or joint pain
- increase in blood sugar (hyperglycemia)
- changes in certain blood tests

ZYNLONTA may cause fertility problems in males which may affect your ability to father children. Talk to your healthcare provider if this is a concern for you.
These are not all of the possible side effects of ZYNLONTA. Call your healthcare provider for medical advice about side effects. You may report side effects to FDA at 1-800-FDA-1088.

General information about the safe and effective use of ZYNLONTA.
Medicines are sometimes prescribed for purposes other than those listed in a Patient Information leaflet. You can ask your healthcare provider or pharmacist for information about ZYNLONTA that is written for healthcare professionals.

What are the ingredients in ZYNLONTA?

Active ingredient: loncastuximab tesirine-lpyl
Inactive ingredients: L-histidine, L-histidine monohydrochloride, polysorbate 20, and sucrose.

Manufactured by: ADC Therapeutics SA, Route de la Corniche 3B, 1066 Epalinges, Switzerland
U.S. license number 2166

Distributed by: ADC Therapeutics America, Murray Hill, New Jersey 07974

ZYNLONTA is a registered trademark of ADC Therapeutics SA

For more information, go to www.ZYNLONTA.com or call 1-855-690-0340

This Patient Information has been approved by the U.S. Food and Drug Administration.

Revised: Feb 2026

PRINCIPAL DISPLAY PANEL - 10 mg Vial Carton

NDC 79952-110-01

Zynlonta®
(loncastuximab tesirine-lpyl)
For Injection

10 mg/vial

For Intravenous Infusion Only

Reconstitute and dilute
prior to administration

One Single-Dose Vial

Discard unused portion

CAUTION: Hazardous Agent

Rx Only

ADC™
THERAPEUTICS